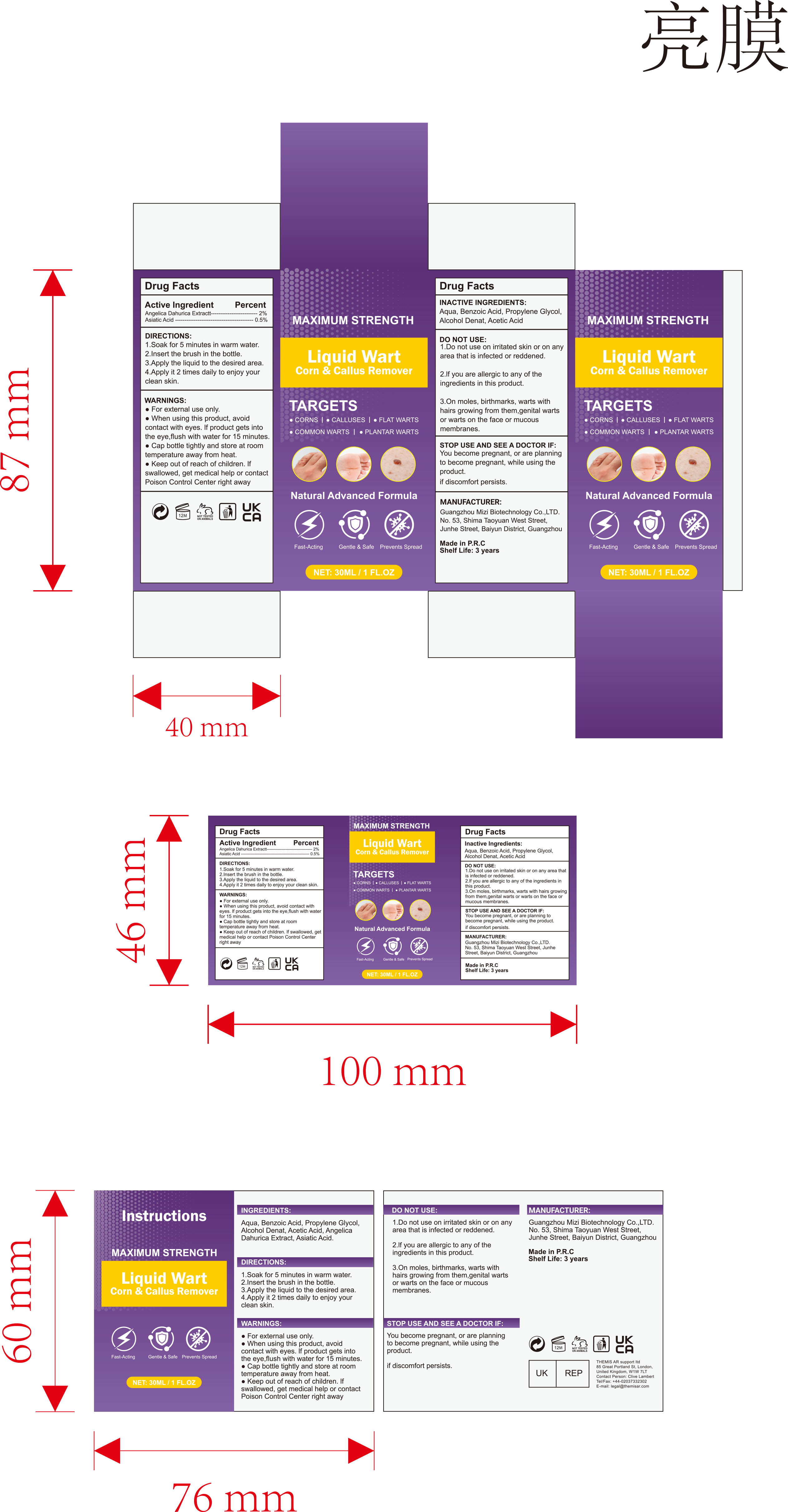 DRUG LABEL: liquid Wart Corn Callus Remover
NDC: 84896-002 | Form: LIQUID
Manufacturer: Guangzhou Mizi Biotechnology Co., LTD.
Category: otc | Type: HUMAN OTC DRUG LABEL
Date: 20251217

ACTIVE INGREDIENTS: ANGELICA DAHURICA ROOT 0.02 g/1 mL; ASIATIC ACID 0.005 g/1 mL
INACTIVE INGREDIENTS: ALCOHOL; ACETIC ACID; BENZOIC ACID; PROPYLENE GLYCOL; AQUA

84896-002 Liquid Wart Corn & Callus Remover

ACTIVE INGREDIENT

ANGELICA DAHURICA ROOT 2%
ASIATIC ACID 0.5%

PURPOSE

wart removal

INDICATIONS AND USAGE

Liquid Wart Corn & Callus Remover

WARNINGS

For external use only.

DO NOT USE

1.Do not use on irritated skin or on any area that is infected or reddened.
2.lf you are allergic to any of the ingredients in this product.
3.On moles, birthmarks, warts with hairs growing from them,genital warts or warts on the face or mucous membranes

When using this product, avoid contact with eyes. lf product gets into the eye,flush with water for 15 minutes
Cap bottle tightly and store at room temperature away from heat.

STOP USE AND SEE A DOCTOR IF:
You become pregnant, or are planning to become pregnant, while using the product.
if discomfort persists.

Keep out of reach of children. lf swallowed, get medical help or contact Poison Control Center right away

DOSAGE AND ADMINISTRATION

1.Soak for 5 minutes in warm water.
2.Insert the brush in the bottle
3.Apply the liquid to the desired area.
4.Apply it 2 times daily to enjoy your clean skin.

INACTIVE INGREDIENT

Aqua, Benzoic Acid, Propylene Glycol, Alcohol Denat, Acetic Acid